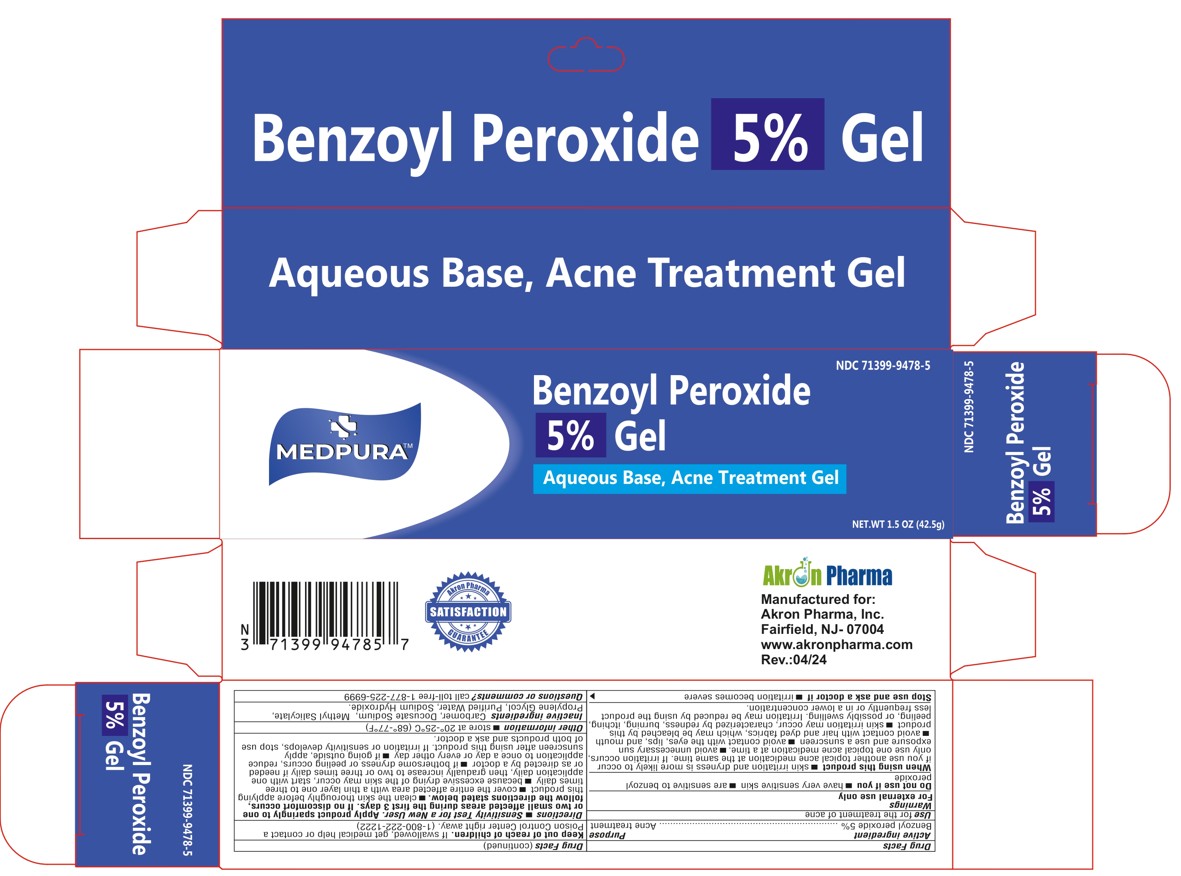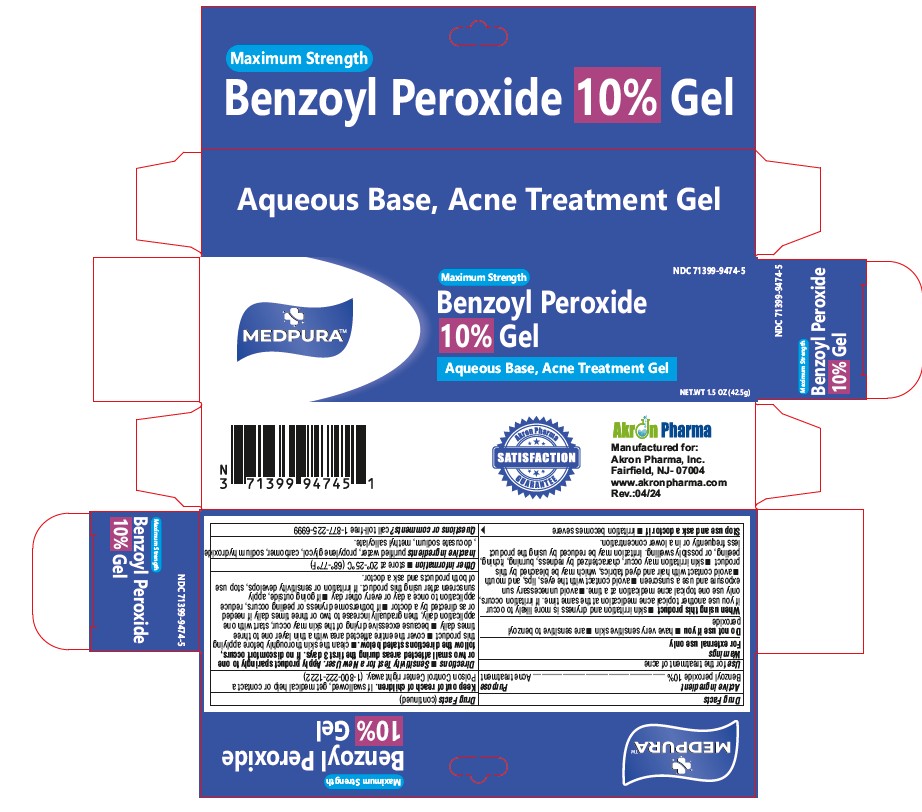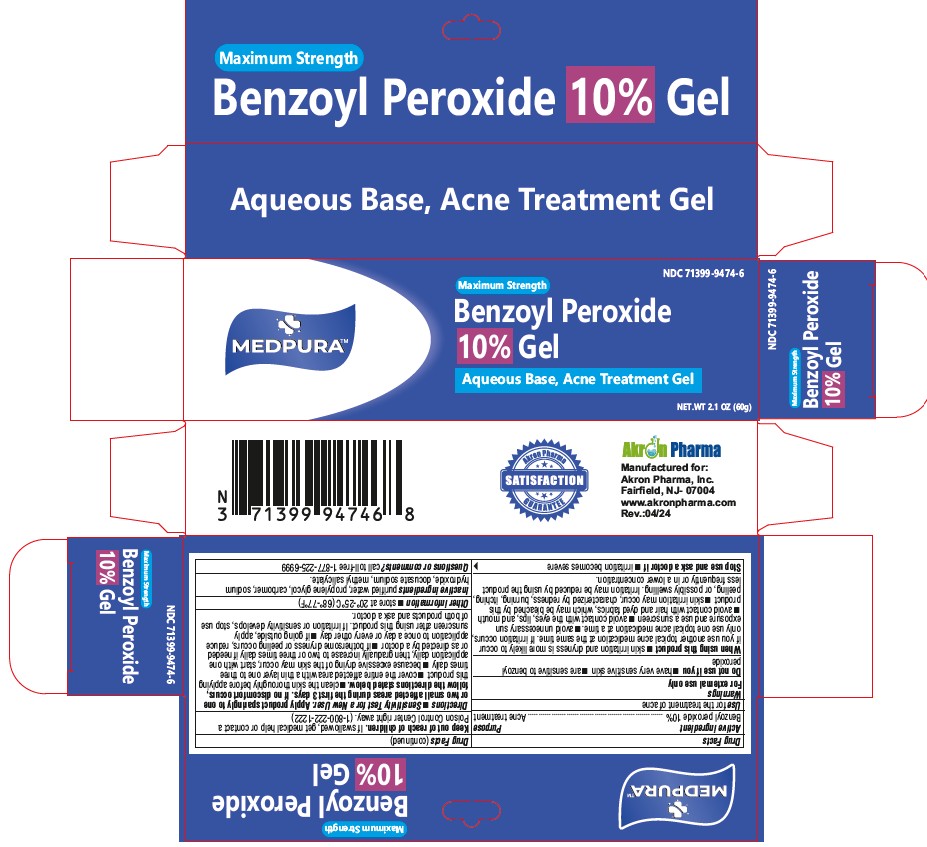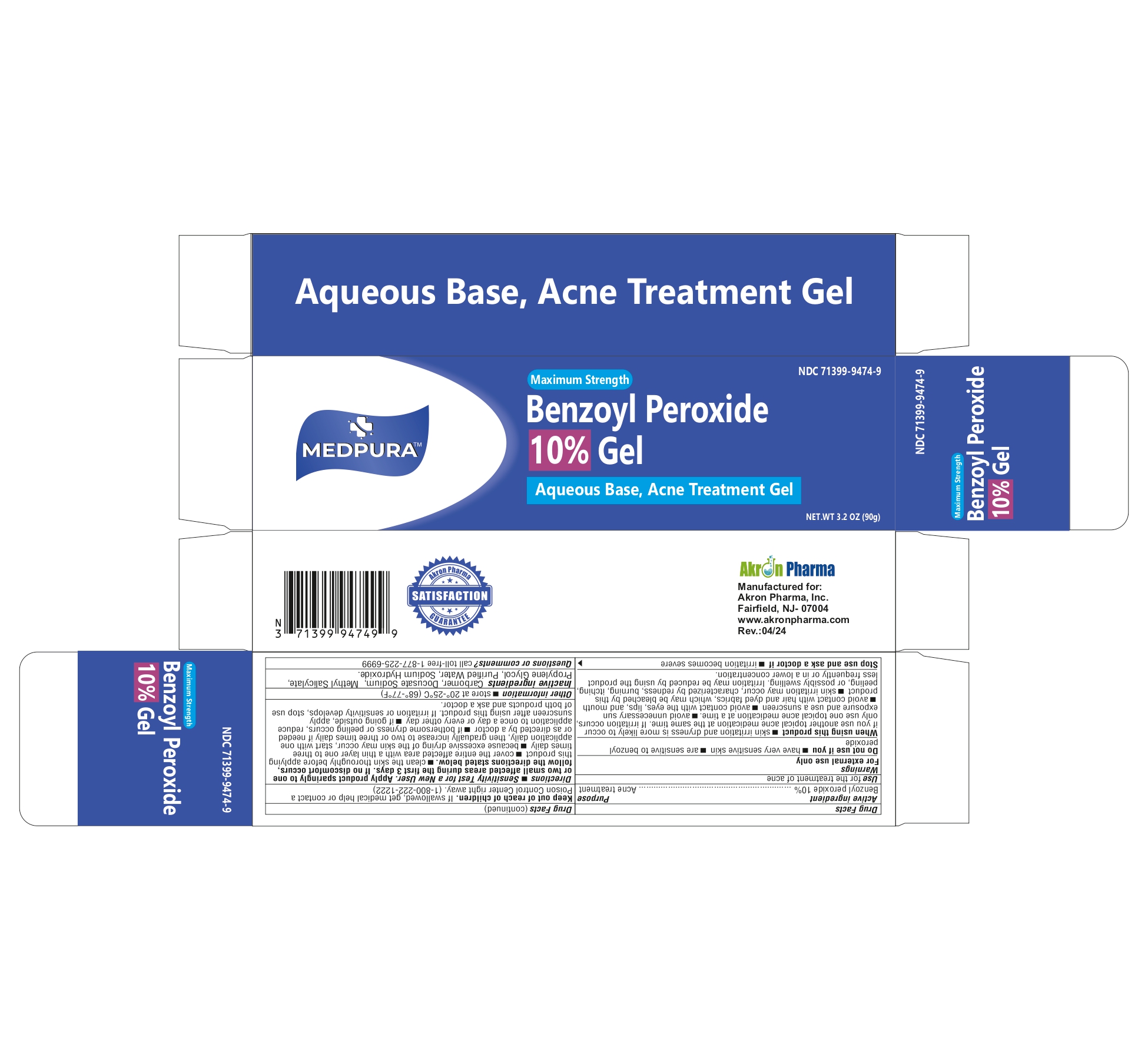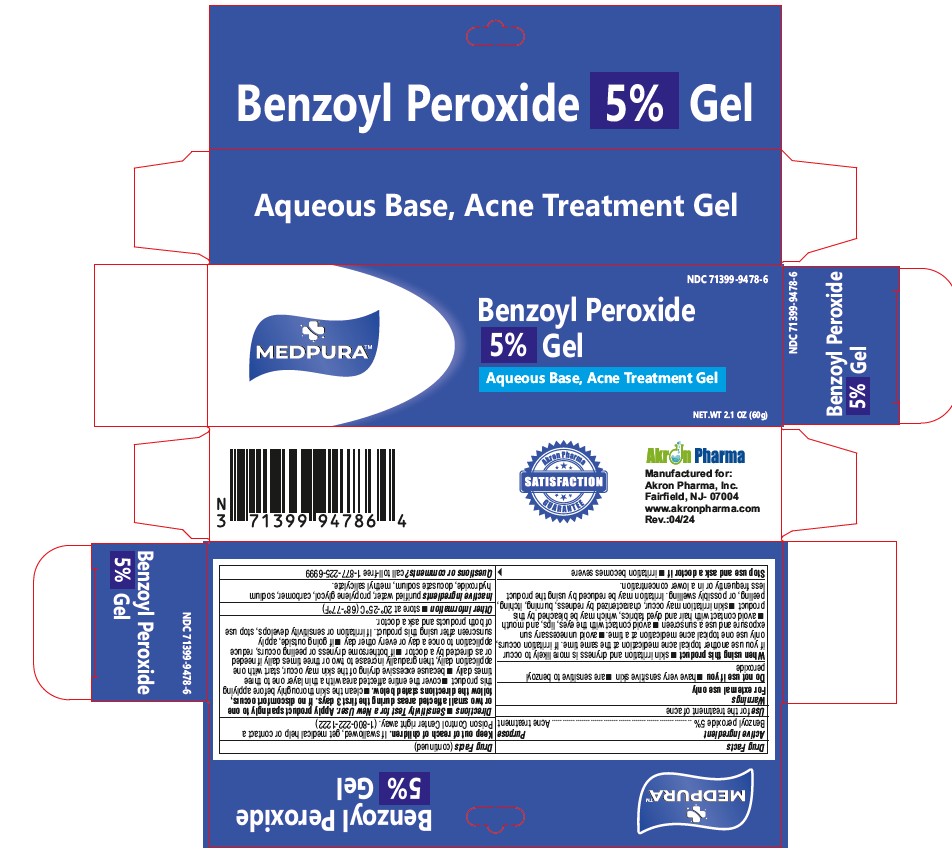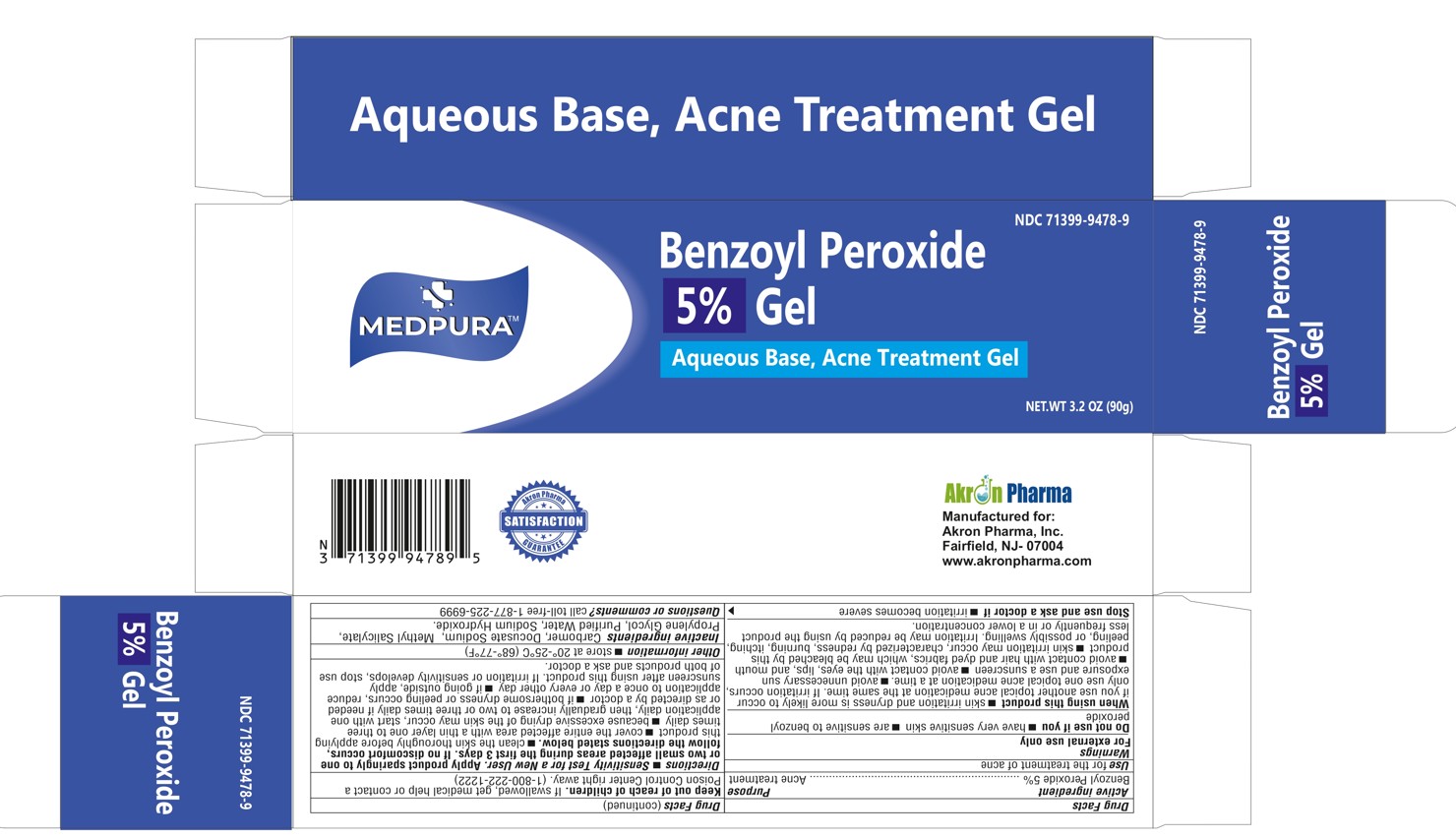 DRUG LABEL: MEDPURA Benzoyl Peroxide
NDC: 71399-9478 | Form: GEL
Manufacturer: Akron Pharma Inc.
Category: otc | Type: HUMAN OTC DRUG LABEL
Date: 20260123

ACTIVE INGREDIENTS: BENZOYL PEROXIDE 50 mg/1 mL
INACTIVE INGREDIENTS: DOCUSATE SODIUM; CARBOMER 980; METHYL SALICYLATE; PROPYLENE GLYCOL; WATER; SODIUM HYDROXIDE

MEDPURA 5% and 10% Benzoyl Peroxide
Aqueous Base, Acne Treatment Gel

Drug Facts

Active ingredient

Benzoyl peroxide 5%

Benzoyl peroxide 10%

Purpose

Acne treatment

Use

for the treatment of acne

Warnings

For external use only

Do not use this medication if you have very sensitive skin or if you are sensitive to benzoyl peroxide.

When using this product

- skin irritation and dryness is more likely to occur if you use another topical acne medication at the same time.
- If irritation occurs, only use one topical acne medication at a time.
- avoid unnecessary sun exposure and use a sunscreen
- avoid contact with the eyes, lips, and mouth
- avoid contact with hair and dyed fabrics, which may be bleached by this product
- skin irritation may occur, characterized by redness, burning, itching, peeling, or possibly swelling. Irritation may be reduced by using the product
- less frequently or in a lower concentration.

Keep out of reach of children. If swallowed, get medical help or contact a Poison Control Center right away. (1-800-222-1222)

Directions

- Sensitivity Test for a New User. Apply product sparingly to one or two small affected areas during the first 3 days. If no discomfort occurs, follow the directions stated below.
- clean the skin thoroughly before applying this product
- cover the entire affected area with a thin layer one to three times daily
- because excessive drying of the skin may occur, start with one application daily, then gradually increase to two or three times daily if needed or as directed by a doctor
- if bothersome dryness or peeling occurs, reduce application to once a day or every other day
- if going outside, apply sunscreen after using this product. If irritation or sensitivity develops, stop use of both products and ask a doctor.

Other information

store at 20°-25°C (68°-77°F)

Inactive ingredients

carbomer, docusate sodium, methyl salicylate, purified water, propylene glycol, sodium hydroxide,

Questions or comments?

call toll-free 1-877-225-6999

Manufactured for:

Akron Pharma, Inc.
Fairfield, NJ-07004
www.akronpharma.com